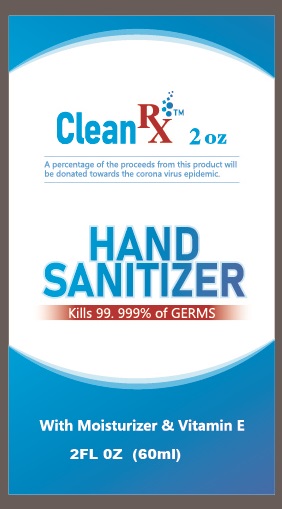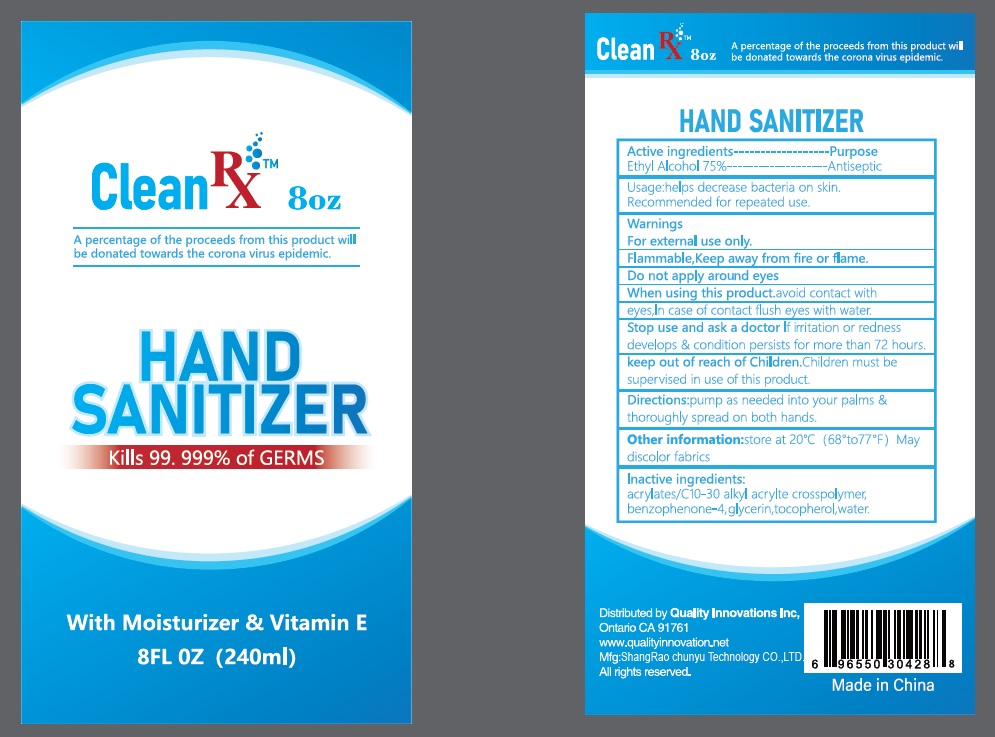 DRUG LABEL: Clean Rx
NDC: 74235-750 | Form: SOLUTION
Manufacturer: Quality Innovations Inc.
Category: otc | Type: HUMAN OTC DRUG LABEL
Date: 20200810

ACTIVE INGREDIENTS: ALCOHOL 75 mL/100 mL
INACTIVE INGREDIENTS: GLYCERIN; SULISOBENZONE; WATER; TOCOPHEROL

Active Ingredient(s)

Ethyl Alcohol 75%

Purpose

Antiseptic

Use

Helps decrease bacteria on skin. Recommended for repeated use.

Warnings

For external use only. Flammable. Keep away from fire or flame

Do not apply

around eyes

When using this product

avoid contact with eyes. In case of contact flush eyes with water.

Stop use and ask a doctor

If irritation or redness develop and conditions persists for more than 72 hours.

Keep out of reach of children.

If swallowed, get medical help or contact a Poison Control Center right away. Children must be supervised in use of this product.

Directions

pump as needed into your palmsand throughly spread on both the hands.

Other information

- Store at 20°C (68° to 77°F).
- May discolor fabrics

Inactive ingredients

acrlates/C10-30 alkyl acrylates crosspolymer, benzophenone-4, glycerin, tocopherol, water

Principal Display Panel

NDC: 74235-750-02

Clean RxTM 2 oz

A percentage of the proceeds from this product will be donated towards the coronavirus epidemic

HAND SANITIZER

Kills 99.999% of GERMS

With Moisturizer and Vitamin E

2 FL OZ (60 mL)

NDC: 74235-750-08

Clean RxTM 8 oz

A percentage of the proceeds from this product will be donated towards the coronavirus epidemic

HAND SANITIZER

Kills 99.999% of GERMS

With Moisturizer and Vitamin E

8 FL OZ (240 mL)